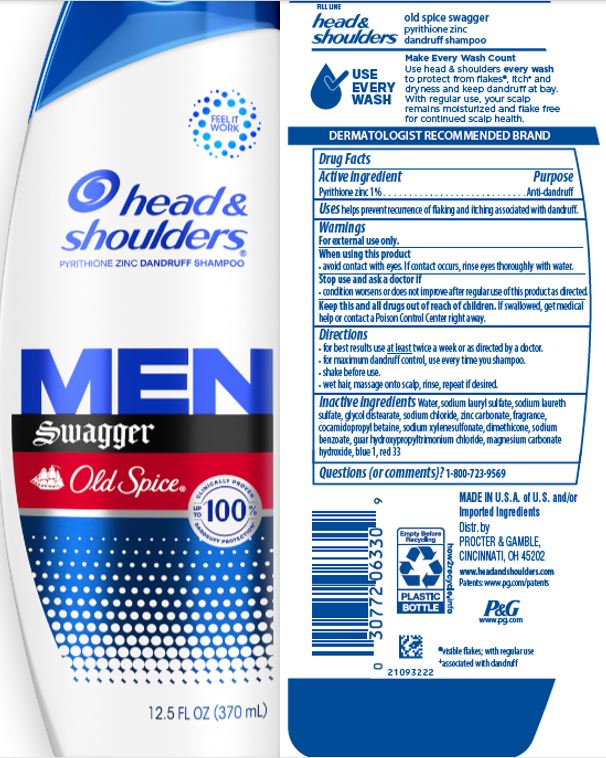 DRUG LABEL: Head and Shoulders Men Advanced Series Swagger Old Spice
NDC: 69423-326 | Form: SHAMPOO
Manufacturer: The Procter & Gamble Manufacturing Company
Category: otc | Type: HUMAN OTC DRUG LABEL
Date: 20251218

ACTIVE INGREDIENTS: PYRITHIONE ZINC 1 g/100 mL
INACTIVE INGREDIENTS: WATER; SODIUM LAURETH-3 SULFATE; GLYCOL DISTEARATE; ZINC CARBONATE; SODIUM CHLORIDE; SODIUM XYLENESULFONATE; COCAMIDOPROPYL BETAINE; DIMETHICONE; SODIUM BENZOATE; MAGNESIUM CARBONATE HYDROXIDE; METHYLCHLOROISOTHIAZOLINONE; METHYLISOTHIAZOLINONE; FD&C BLUE NO. 1; D&C RED NO. 33; GUAR HYDROXYPROPYLTRIMONIUM CHLORIDE (1.7 SUBSTITUENTS PER SACCHARIDE); SODIUM LAURYL SULFATE

Head and Shoulders® Men Advanced Series Swagger Old Spice Shampoo

Drug Facts

Active ingredient

Pyrithione zinc 1%

Purpose

Anti-dandruff

Uses

helps prevent recurrence of flaking and itching associated with dandruff.

Warnings

For external use only.

When using this product

- avoid contact with eyes. If contact occurs, rinse eyes thoroughly with water.

Stop use and ask a doctor if

- condition worsens or does not improve after regular use of this product as directed.

KEEP OUT OF REACH OF CHILDREN

Keep this and all drugs out of reach of children. If swallowed, get medical help or contact a Poison Control Center right away.

Directions

- for best results use at least twice a week or as directed by a doctor.
- for maximum dandruff control, use every time you shampoo.
- shake before use.
- wet hair, massage onto scalp, rinse, repeat if desired.

Inactive ingredients

Water, sodium lauryl sulfate, sodium laureth sulfate, glycol distearate, sodium chloride, zinc carbonate, fragrance, cocamidopropyl betaine, sodium xylenesulfonate, dimethicone, sodium benzoate, guar hydroxypropyltrimonium chloride, magnesium carbonate hydroxide, blue 1, red 33

Questions (or comments)?

1-800-723-9569

Dist. by PROCTER & GAMBLE,
CINCINNATI, OH 45202

PRINCIPAL DISPLAY PANEL - 370 mL Bottle Label

head &

shoulders

PYRITHIONE ZINC DANDRUFF

SHAMPOO

MEN

SWAGGER

Old Spice

FLAKE FREE

UP TO 100%

GUARANTEED

12.5 FL OZ (370 mL)